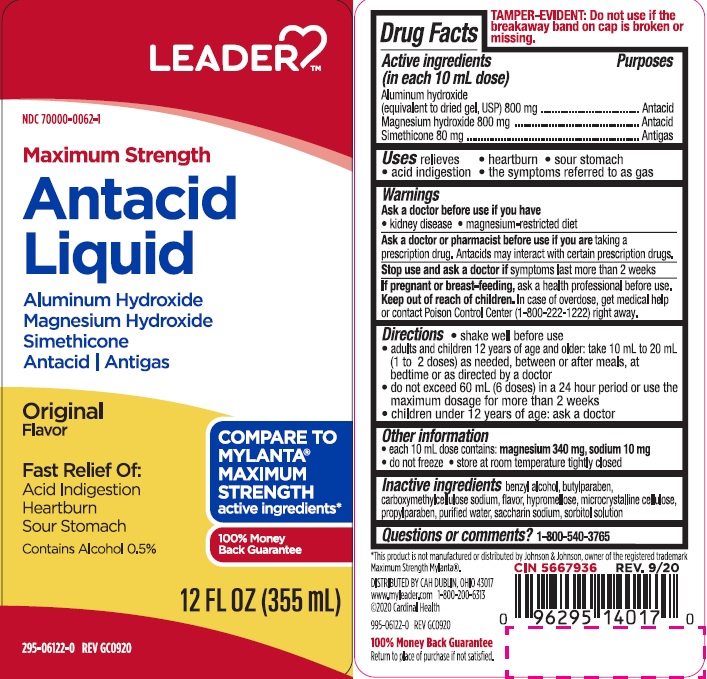 DRUG LABEL: MAXIMUM STRENGTH ANTACID
NDC: 70000-0062 | Form: SUSPENSION
Manufacturer: CARDINAL HEALTH
Category: otc | Type: HUMAN OTC DRUG LABEL
Date: 20231107

ACTIVE INGREDIENTS: ALUMINUM HYDROXIDE 800 mg/10 mL; MAGNESIUM HYDROXIDE 800 mg/10 mL; DIMETHICONE 80 mg/10 mL
INACTIVE INGREDIENTS: BENZYL ALCOHOL; BUTYLPARABEN; CARBOXYMETHYLCELLULOSE SODIUM; HYPROMELLOSES; CELLULOSE, MICROCRYSTALLINE; PROPYLPARABEN; WATER; SACCHARIN SODIUM; SORBITOL SOLUTION

ldr max antacid

Active ingredients (in each 10 mL dose)

Aluminum hydroxide 800 mg (equivalent to dried gel, USP)

Magnesium hydroxide 800 mg

Simethicone 80 mg

Purposes

Antacid

Antigas

Uses

relieves

- heartburn
- sour stomach
- acid indigestion
- the symptoms referred to as gas

Warnings

Ask a doctor before use if you have

- kidney disease
- a magnesium-restricted diet

Ask a doctor or pharmacist before use if you are taking a prescription drug.

Antacids may interact with certain prescription drugs.

Stop use and ask a doctor if symptoms last more than 2 weeks

If pregnant or breast-feeding, ask a health professional before use.

Keep out of reach of children. In case of overdose, get medical help
or contact Poison Control Center (1-800-222-1222) right away.

Directions

- shake well before use
- adults and children 12 years and older: take 10 mL to 20 mL(1 to 2 doses) as needed, between or after meals, at bedtime or as directed by a doctor
- do not exceed 60 mL (6 doses) in a 24 hour period or use the maximum dosage for more than 2 weeks
- children under 12 years of age: ask a doctor

Other information

- each 10 mL teaspoonful contains: magnesium 340 mg, sodium 10 mg
- do not freeze
- store at room temperature tightly closed

Inactive ingredients

benzyl alcohol, butylparaben, carboxymethylcellulose sodium, flavor (contains alcohol), hypromellose, microcrystalline cellulose, propylparaben, purified water, saccharin sodium, sorbitol solution

Questions or comments?

1-800-540-3765